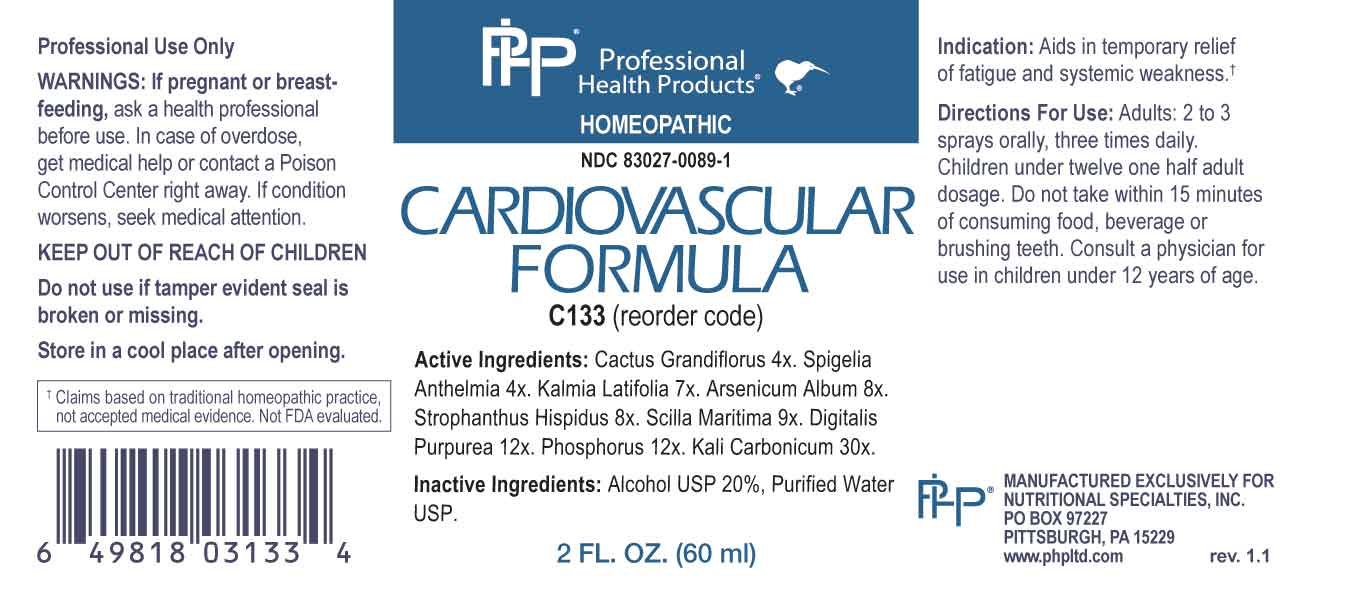 DRUG LABEL: Cardiovascular Formula
NDC: 83027-0089 | Form: SPRAY
Manufacturer: Nutritional Specialties, Inc.
Category: homeopathic | Type: HUMAN OTC DRUG LABEL
Date: 20230922

ACTIVE INGREDIENTS: SELENICEREUS GRANDIFLORUS STEM 4 [hp_X]/1 mL; SPIGELIA ANTHELMIA WHOLE 4 [hp_X]/1 mL; KALMIA LATIFOLIA LEAF 7 [hp_X]/1 mL; ARSENIC TRIOXIDE 8 [hp_X]/1 mL; STROPHANTHUS HISPIDUS SEED 8 [hp_X]/1 mL; DRIMIA MARITIMA BULB 9 [hp_X]/1 mL; DIGITALIS 12 [hp_X]/1 mL; PHOSPHORUS 12 [hp_X]/1 mL; POTASSIUM CARBONATE 30 [hp_X]/1 mL
INACTIVE INGREDIENTS: WATER; ALCOHOL

DRUG FACTS:

ACTIVE INGREDIENTS:

Cactus Grandiflorus 4X, Spigelia Anthelmia 4X, Kalmia Latifolia 7X , Arsenicum Album 8X, Strophanthus Hispidus 8X, Scilla Maritima 9X, Digitalis Purpurea 12X, Phosphorus 12X, Kali Carbonicum 30X.

PURPOSE:

Aids in temporary relief of fatigue and systemic weakness.†

†Claims based on traditional homeopathic practice, not accepted medical evidence. Not FDA evaluated.

WARNINGS:

Professional Use Only

If pregnant or breast-feeding, ask a health professional before use.

In case of overdose, get medical help or contact a Poison Control Center right away.

If condition worsens, seek medical attention.

KEEP OUT OF REACH OF CHILDREN

Do not use if tamper evident seal is broken or missing.

Store in a cool place after opening

KEEP OUT OF REACH OF CHILDREN:

In case of overdose, get medical help or contact a Poison Control Center right away.

DIRECTIONS:

Adults: 2 to 3 sprays orally, three times daily. Children under twelve one half adult dosage. Do not take within 15 minutes of consuming food, beverage or brushing teeth. Consult a physician for use in children under 12 years of age.

INDICATIONS:

Aids in temporary relief of fatigue and systemic weakness.†

†Claims based on traditional homeopathic practice, not accepted medical evidence. Not FDA evaluated.

INACTIVE INGREDIENTS:

Alcohol USP 20%, Purified Water USP.

QUESTIONS:

MANUFACTURED EXCLUSIVELY FOR

NUTRITIONAL SPECIALTIES, INC.

PO BOX 97227

PITTSBURG, PA 15229

www.phpltd.com

PACKAGE LABEL DISPLAY:

Professional

Health Products

HOMEOPATHIC

NDC 83027-0089-1

CARDIOVASCULAR

FORMULA

2 FL. OZ (60 ml)